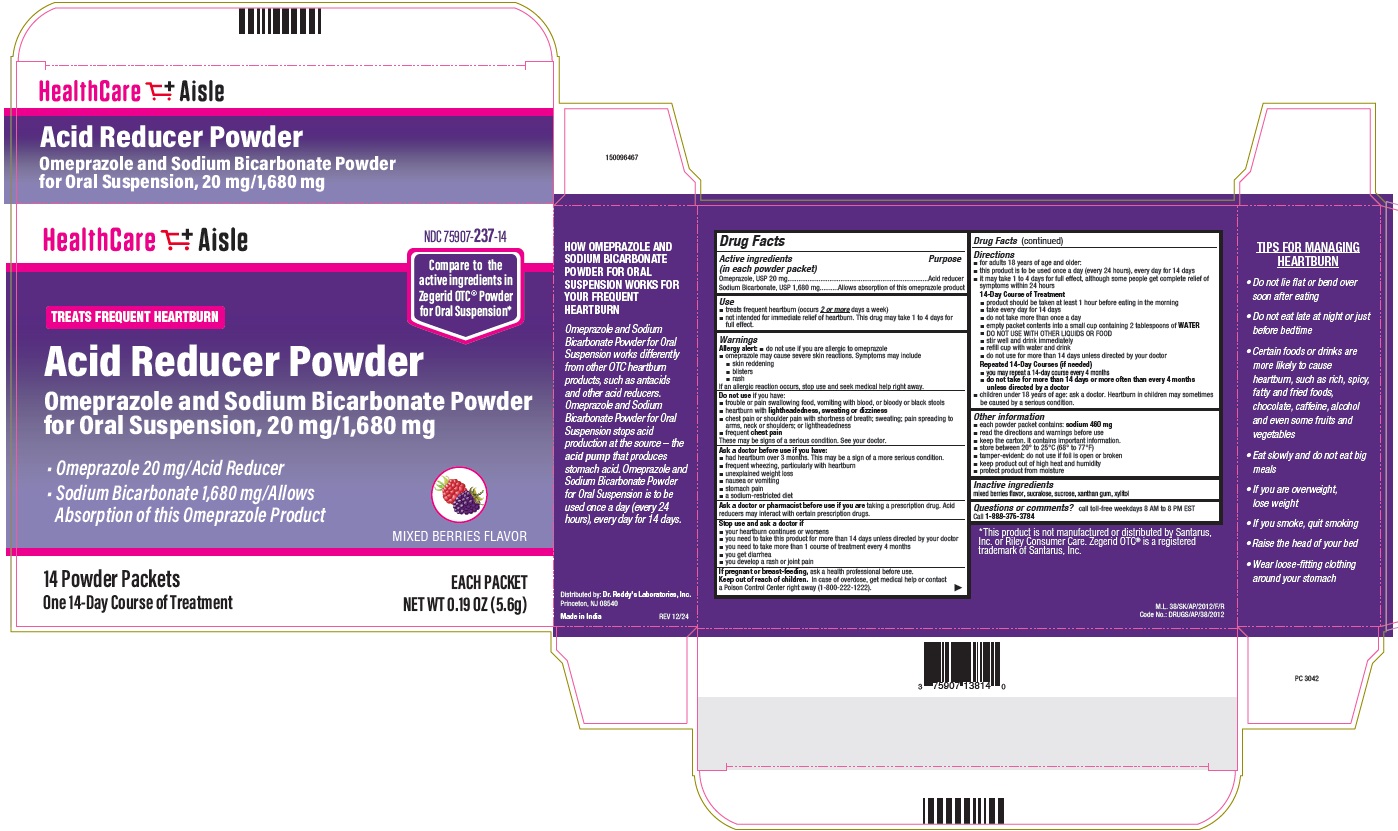 DRUG LABEL: Acid Reducer Powder
NDC: 75907-237 | Form: POWDER, FOR SUSPENSION
Manufacturer: Dr. Reddy's Laboratories Inc.,
Category: otc | Type: HUMAN OTC DRUG LABEL
Date: 20250303

ACTIVE INGREDIENTS: OMEPRAZOLE 20 mg/1 1; SODIUM BICARBONATE 1680 mg/1 1
INACTIVE INGREDIENTS: SUCRALOSE; SUCROSE; XANTHAN GUM; XYLITOL

Drug Facts

Active ingredient(s)

Active ingredients

(in each powder packet)

Omeprazole, USP 20 mg....................................Acid Reducer

Sodium Bicarbonate, USP 1,680 mg..................Allows absorption of this omeprazole product

Purpose

Acid reducer

Allows absorption of this omeprazole product

Use(s)

- treats frequent heartburn (occurs 2 or more days a week)
- not intended for immediate relief of heartburn. This drug may take 1 to 4 days for full effect.

Warnings

Allergy alert:

- do not use if you are allergic to omeprazole
- omeprazole may cause severe skin reactions. Symptoms may include
- skin reddening
- blisters
- rash.
  If an allergic reaction occurs, stop use and seek medical help right away.

Do not use if you have:

- trouble or pain swallowing food, vomiting with blood, or bloody or black stools
- heartburn with lightheadedness, sweating, or dizziness
- chest pain or shoulder pain with shortness of breath; sweating; pain spreading to arms, neck or shoulders; or lightheadedness
- frequent chest pain
  These may be signs of a serious condition. See your doctor.

Ask a doctor before use if you have:

- had heartburn over 3 months. This may be a sign of a more serious condition.
- frequent wheezing, particularly with heartburn
- unexplained weight loss
- nausea or vomiting
- stomach pain
- a sodium-restricted diet

Ask a doctor or pharmacist before use if

you are taking a prescription drug. Acid reducers may interact with certain prescription drugs.

Stop use and ask doctor if

- your heartburn continues or worsens
- you need to take this product for more than 14 days unless directed by your doctor
- you need to take more than 1 course of treatment every 4 months
- you get diarrhea
- you develop a rash or joint pain

PREGNANCY OR BREAST FEEDING

If pregnant or breast-feeding, ask a health professional before use.

Keep out of reach of children

In case of overdose, get medical help or contact a Poison Control Center right away (1-800-222-1222).

Directions

- for adults 18 years of age and older:
- this product is to be used once a day (every 24 hours), every day for 14 days
- it may take 1 to 4 days for full effect, although some people get complete relief of symptoms within 24 hours
  14-Day Course of Treatment
- product should be taken at least 1 hour before eating in the morning
- take every day for 14 days
- do not take more than once a day
- empty packet contents into a small cup containing 2 tablespoons of WATER
- DO NOT USE WITH OTHER LIQUIDS OR FOOD
- stir well and drink immediately
- refill cup with water and drink
- do not use for more than 14 days unless directed by your doctor

Repeated 14-Day Courses (if needed)

- you may repeat a 14-day course every 4 months
- do not take for more than 14 days or more often than every 4 months unless directed by a doctor
- children under 18 years of age: ask a doctor. Heartburn in children may sometimes be caused by a serious condition.

Other information

- each powder packet contains: sodium 460 mg
- read the directions and warnings before use
- keep the carton. It contains important information
- store between 20° to 25 °C (68° to 77°F)
- tamper-evident: do not use if foil is open or broken
- keep product out of high heat and humidity
- protect product from moisture

Inactive ingredients

mixed berries flavor, sucralose, sucrose, xanthan gum, xylitol

Questions or comments?

call toll-free weekdays 8 AM to 8 PM EST Call 1-888-375-3784

TIPS FOR MANAGING HEARTBURN

- Do not lie flat or bend over soon after eating
- Do not eat late at night or just before bedtime
- Certain foods or drinks are more likely to cause heartburn, such as rich, spicy, fatty and fried foods, chocolate, caffeine, alcohol and even some fruits and vegetables
- Eat slowly and do not eat big meals
- If you are oveweight, lose weight
- If you smoke, quit smoking
- Raise the head of your bed
- Wear loose-fitting clothing around your stomach

HOW OMEPRAZOLE AND SODIUM BICARBONATE POWDER FOR ORAL SUSPENSION WORKS FOR YOUR FREQUENT HEARTBURN

Omeprazole and Sodium Bicarbonate Powder for Oral Suspension works differently from other OTC heartburn products, such as antacids and other acid reducers. Omeprazole and Sodium Bicarbonate Powder for Oral Suspension stops acid production at the source – the acid pump that produces stomach acid. Omeprazole and Sodium Bicarbonate Powder for Oral Suspension is to be used once a day (every 24 hours), every day for 14 days.

*This product is not manufactured or distributed by Santarus, Inc. or Riley Consumer Care. Zegerid OTC® is a registered trademark of Santarus, Inc.

Distributed by:

Dr. Reddy's Laboratories, Inc.

Princeton, NJ 08540

Made in India

Principal Display Panel

Omeprazole 20 mg /Acid Reducer

Sodium Bicarbonate 1,680 mg/Allows Absorption of this Omeprazole Product